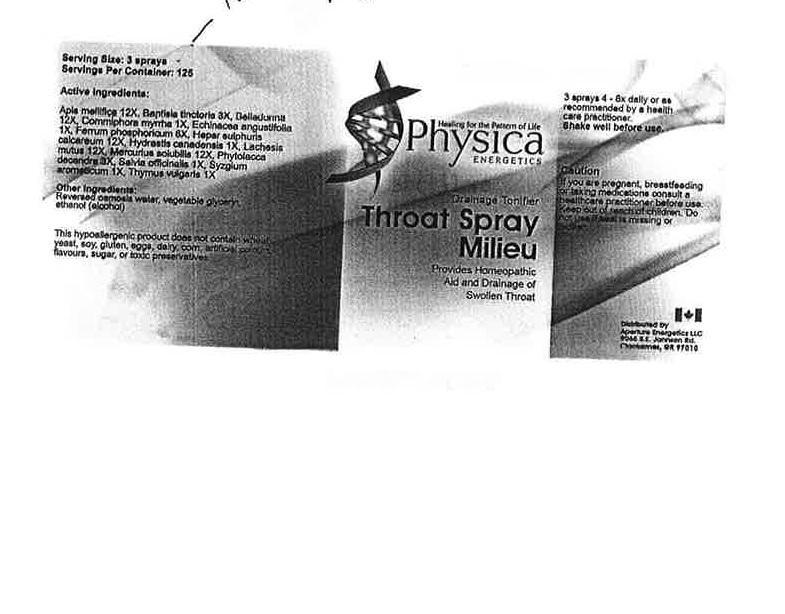 DRUG LABEL: Throat Milieu
NDC: 54118-7114 | Form: SOLUTION/ DROPS
Manufacturer: ABCO labratories, Inc.
Category: homeopathic | Type: HUMAN OTC DRUG LABEL
Date: 20150824

ACTIVE INGREDIENTS: APIS MELLIFERA 12 [hp_X]/60 mL; BAPTISIA TINCTORIA 3 [hp_X]/60 mL; BELLADONNA LEAF 12 [hp_X]/60 mL; COMMIPHORA MYRRHA WHOLE 1 [hp_X]/60 mL; ECHINACEA ANGUSTIFOLIA 1 [hp_X]/60 mL; FERRIC PHOSPHATE 6 [hp_X]/60 mL; CALCIUM SULFIDE 12 [hp_X]/60 mL; HYDRASTIS CANADENSIS WHOLE 1 [hp_X]/60 mL; LACHESIS MUTA WHOLE 12 [hp_X]/60 mL; MERCURIUS SOLUBILIS 12 [hp_X]/60 mL; PHYTOLACCA AMERICANA WHOLE 3 [hp_X]/60 mL; SALVIA OFFICINALIS WHOLE 1 [hp_X]/60 mL; CLOVE 1 [hp_X]/60 mL; THYMUS VULGARIS WHOLE 1 [hp_X]/60 mL
INACTIVE INGREDIENTS: WATER; ALCOHOL; GLYCERIN

Throat Milieu

WARNINGS

If you are pregnant, breastfeeding or taking medications consult a health care practitioner before use.

keep out of reach of children.

Do not use if seal is missing or broken.

Keep out of reach of children.

INDICATIONS AND USAGE

Drainage Tonifier

PURPOSE

Provides Homeopathic Aid and Drainage of Swollen Throat

DOSAGE AND ADMINISTRATION

3 sprays 4-6x daily or as recommended by a health care practitioner.

Shake well before use.

INACTIVE INGREDIENT

Reversed osmosis water, vegetable glycerin, alcohol (ethanol).

ACTIVE INGREDIENT

Apis Mellifica 12x, Baptisia Tinctoria 3x, Belladonna 12x, Commiphora Myrrha 1x, Echinacea Angustifolia 1x, Ferrum Phosphate 6x, Hepar Sulphuris Calcareum 12x, Hydrastis Canadensis 1x, Lachesis Muta 12x, Mercurius Solubilis 12x, Phytolacca Decandra 3x, Salvia Officinalis 1x, Syzgium Aromaticum 1x, Thymus Vulgaris 1x.